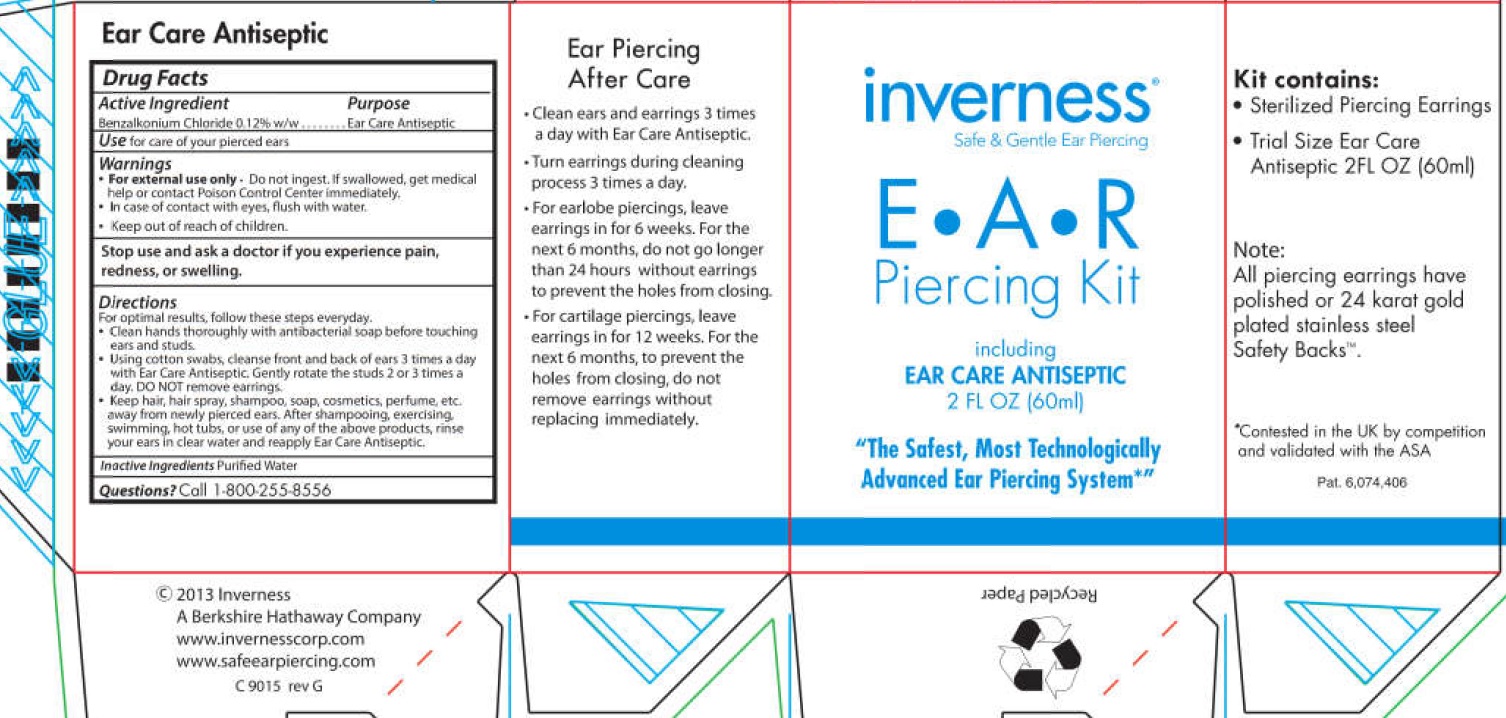 DRUG LABEL: Inverness Ear Piercing
NDC: 70094-002 | Form: KIT | Route: TOPICAL
Manufacturer: The Richline Group, Inc.
Category: otc | Type: HUMAN OTC DRUG LABEL
Date: 20231108

ACTIVE INGREDIENTS: BENZALKONIUM CHLORIDE 1.2 mg/1 mL
INACTIVE INGREDIENTS: WATER

Active Ingredient

Benzalkonium Chloride 0.12% w/w

Purpose

Ear Care Antiseptic

Use

for care of your pierced ears

Warnings

- For external use only. Do not ingest. If swallowed, get medical help or contact Poison Control Center immediately.
- In case of contact with eyes, flush with water.

Stop use and ask a doctor

if you experience pain, redenss, or swelling.

Directions

For optimal results, follow these steps everday.

- Clean hands thoroughly with antibacterial soap before touching ears and studs.
- Using cotton swabs, cleanse front and back of ears 3 times a day with Ear Care Antiseptic. Gently rotate the studs 2 or 3 times a day. DO NOT remove earrings.
- Keep hair, hair spray, shampoo, soap, cosmetics, perfume, ets. away from newly pierced ears. After shampooing, exercising, swimming, hot tubs, or use of any of the above products, rinse yours ears in clear water and reapply Ear Care Antiseptic

Inactive Ingredients

Purified Water

Questions?

Call 1-800-255-8556